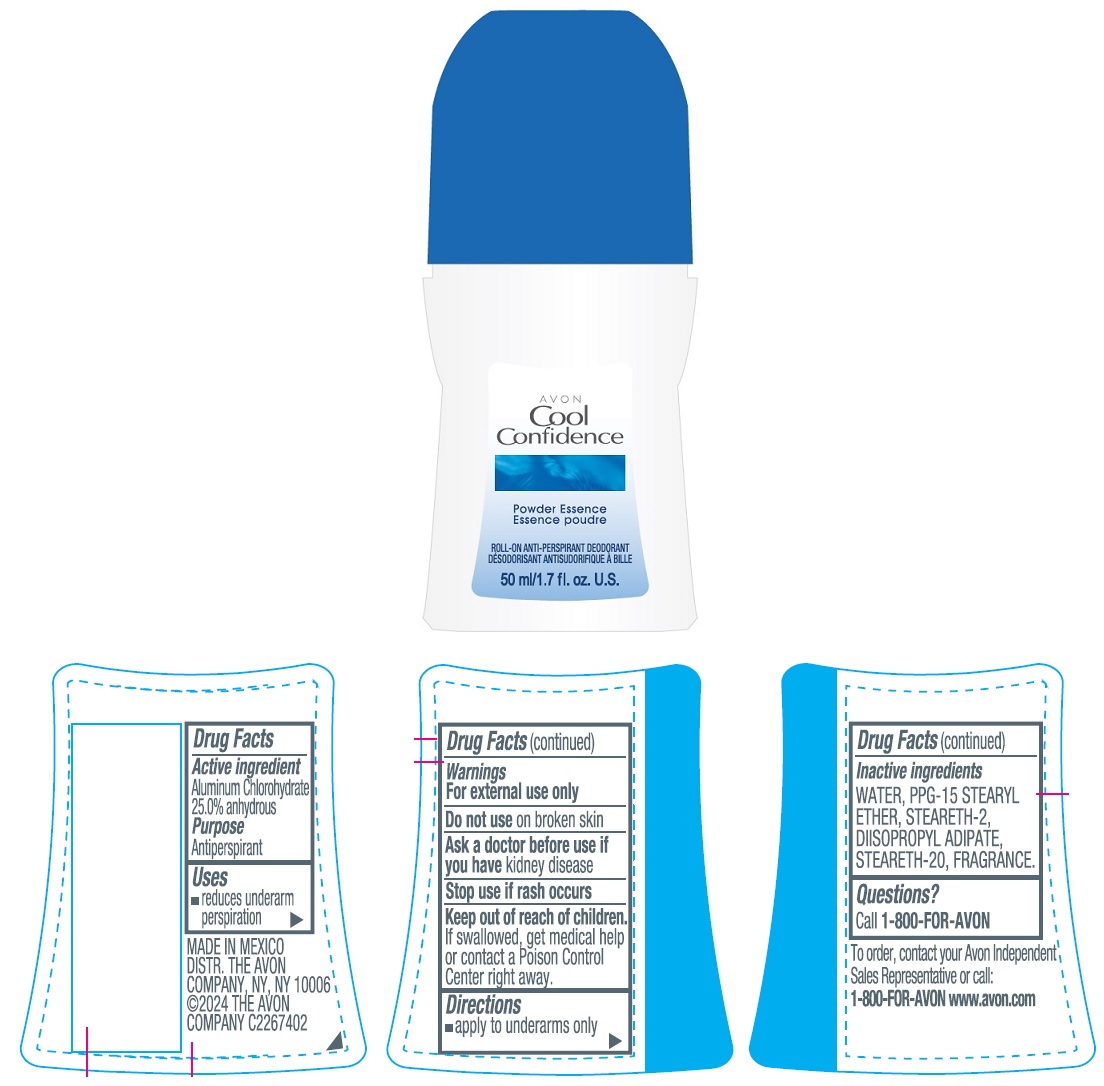 DRUG LABEL: AVON Cool Confidence Powder Essence
NDC: 71110-1510 | Form: STICK
Manufacturer: Avon Cosmetics Manufacturing, S. de R.L. de C.V.
Category: otc | Type: HUMAN OTC DRUG LABEL
Date: 20241112

ACTIVE INGREDIENTS: ALUMINUM CHLOROHYDRATE 250 mg/1 mL
INACTIVE INGREDIENTS: STEARETH-2; WATER; DIISOOCTYL ADIPATE; PPG-15 STEARYL ETHER; STEARETH-20

AVON Cool Confidence Powder Essence Roll-On Anti-Perspirant Deodorant 50ml

Active ingredient

Aluminum Chlorohydrate 25.0% anhydrous

Purpose

Antiperspirant

Uses

- reduces underarm perspiration

Warnings

For external use only

Do not useon broken skin

Ask a doctor before use if you havekidney disease

Stop use if rash occurs

Keep out of reach of children.
If swallowed, get medical help or contact a Poison Control Center right away.

Directions

- apply to underarms only

Inactive ingredients

WATER, PPG-15 STEARYL ETHER, STEARETH-2, DIISOOCTYL ADIPATE, STEARETH-20, FRAGRANCE

Questions?

Call 1-800-FOR-AVON

To order, contact your Avon Independent Sales Representative or call:
1-800-FOR-AVON www.avon.com

MADE IN MEXICO
DIST. THE AVON COMPANY, NY, NY 10006
©2024 THE AVON COMPANY C2267402

Principal Display Panel

AVON
Cool
Confidence
Powder Essence
ROLL-ON ANTI-PERSPIRANT DEODORANT
50 ml/1.7 fl.oz. U.S.